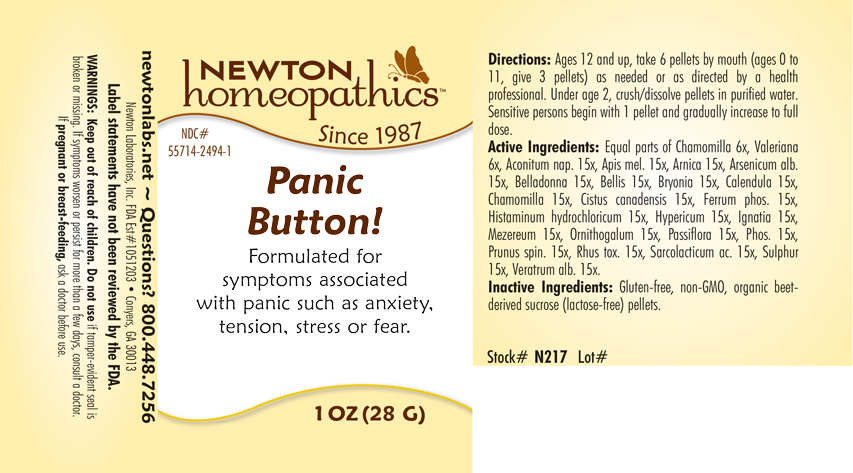 DRUG LABEL: Panic Button
NDC: 55714-2494 | Form: PELLET
Manufacturer: Newton Laboratories, Inc.
Category: homeopathic | Type: HUMAN OTC DRUG LABEL
Date: 20250207

ACTIVE INGREDIENTS: ACONITUM NAPELLUS 15 [hp_X]/1 g; APIS MELLIFERA 15 [hp_X]/1 g; ARNICA MONTANA 15 [hp_X]/1 g; ARSENIC TRIOXIDE 15 [hp_X]/1 g; ATROPA BELLADONNA 15 [hp_X]/1 g; BELLIS PERENNIS 15 [hp_X]/1 g; BRYONIA ALBA ROOT 15 [hp_X]/1 g; CALENDULA OFFICINALIS FLOWERING TOP 15 [hp_X]/1 g; MATRICARIA CHAMOMILLA 15 [hp_X]/1 g; HELIANTHEMUM CANADENSE 15 [hp_X]/1 g; FERROSOFERRIC PHOSPHATE 15 [hp_X]/1 g; HISTAMINE DIHYDROCHLORIDE 15 [hp_X]/1 g; HYPERICUM PERFORATUM 15 [hp_X]/1 g; STRYCHNOS IGNATII SEED 15 [hp_X]/1 g; DAPHNE MEZEREUM BARK 15 [hp_X]/1 g; ORNITHOGALUM UMBELLATUM 15 [hp_X]/1 g; TOXICODENDRON PUBESCENS LEAF 15 [hp_X]/1 g; PASSIFLORA INCARNATA FLOWERING TOP 15 [hp_X]/1 g; PHOSPHORUS 15 [hp_X]/1 g; PRUNUS SPINOSA FLOWER BUD 15 [hp_X]/1 g; LACTIC ACID, L- 15 [hp_X]/1 g; SULFUR 15 [hp_X]/1 g; VERATRUM ALBUM ROOT 15 [hp_X]/1 g; VALERIAN 6 [hp_X]/1 g
INACTIVE INGREDIENTS: SUCROSE

Panic 2494P

INDICATIONS & USAGE SECTION

Formulated for symptoms associated with panic such as anxiety, tension, stress or fear.

DOSAGE & ADMINISTRATION SECTION

Directions: Ages 12 and up, take 6 pellets by mouth (ages 0 to 11, give 3 pellets) as needed or as directed by a health professional. Under age 2, crush/dissolve pellets in purified water. Sensitive persons begin with 1 pellet and gradually increase to full dose.

OTC - ACTIVE INGREDIENT SECTION

Equal parts of Chamomilla 6x, Valeriana officinalis 6x, Aconitum napellus 15x, Apis mellifica 15x, Arnica montana 15x, Arsenicum album 15x, Belladonna 15x, Bellis perennis 15x, Bryonia 15x, Calendula officinalis 15x, Chamomilla 15x, Cistus canadensis 15x, Ferrum phosphoricum 15x, Histaminum hydrochloricum 15x, Hypericum perforatum 15x, Ignatia amara 15x, Mezereum 15x, Ornithogalum umbellatum 15x, Passiflora incarnata 15x, Phosphorus 15x, Prunus spinosa 15x, Rhus toxicodendron 15x, Sarcolacticum acidum 15x, Sulphur 15x, Veratrum album 15x.

OTC - PURPOSE SECTION

Formulated for symptoms associated with panic such as anxiety, tension, stress or fear.

INACTIVE INGREDIENT SECTION

Inactive Ingredients: Gluten-free, non-GMO, organic beet-derived sucrose (lactose-free) pellets.

QUESTIONS SECTION

newtonlabs.net – Questions? 800.448.7256

Newton Laboratories, Inc. FDA Est # 1051203 - Conyers, GA 30013

WARNINGS SECTION

WARNINGS: Keep out of reach of children. Do not use if tamper-evident seal is broken or missing. If symptoms worsen or persist for more than a few days, consult a doctor. If pregnant or breast-feeding, ask a doctor before use.

OTC - PREGNANCY OR BREAST FEEDING SECTION

If pregnant or breast-feeding, ask a doctor before use.

OTC - KEEP OUT OF REACH OF CHILDREN SECTION

Keep out of reach of children.